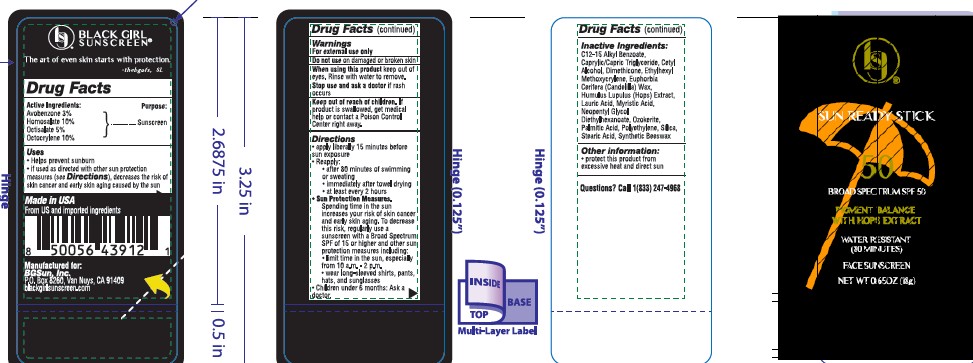 DRUG LABEL: Black Girl Sunscreen SPF 50
NDC: 84204-0015 | Form: STICK
Manufacturer: Black Girl Sunscreen
Category: otc | Type: HUMAN OTC DRUG LABEL
Date: 20250926

ACTIVE INGREDIENTS: HOMOSALATE 10 g/100 g; OCTOCRYLENE 10 g/100 g; OCTISALATE 5 g/100 g; AVOBENZONE 3 g/100 g
INACTIVE INGREDIENTS: C12-15 ALKYL BENZOATE; CAPRYLIC/CAPRIC TRIGLYCERIDE; CETYL ALCOHOL; DIMETHICONE; ETHYLHEXYL METHOXYCRYLENE; EUPHORBIA CERIFERA (CANDELILLA) WAX; HUMULUS LUPULUS WHOLE; LAURIC ACID; MYRISTIC ACID; NEOPENTYL GLYCOL DIETHYLHEXANOATE; CERESIN; PALMITIC ACID; POLYETHYLENE; SILICA; STEARIC ACID; SYNTHETIC BEESWAX

Black Girl Sunscreen SPF 50 Stick

Active ingredients Purpose

Homosalate 10.00%
Octocrylene 10.00% Sunscreen
Octisalate 5.00%
Avobenzone 3.00%

INDICATIONS AND USAGE

Uses■ helps prevent sunburn ■ if used as directed with other sun
protection measures (see Directions), decreases the risk of skin
cancer and early skin aging caused by the sun.

DOSAGE AND ADMINISTRATION

Directions• apply liberally to cool, dry skin
15 minutes before sun exposure • reapply:
• after 80 minutes of swimming or sweating
• immediately after towel drying • at least every 2
hours • Sun Protection Measures. Spending time
in the sun increases your risk of skin cancer and
early skin aging. To decrease this risk, regularly
use a sunscreen with a broad spectrum SPF of 15
or higher and other sun protection measures
including: • limit time in the sun,especially from
10 a.m. - 2. p.m. • wear a long-sleeve shirts,
pants, hats, and sunglasses. • children under 6
months: Ask a doctor.

Warnings
For external use only.
Flammable:Do not use white smoking or near heat or flame.
Do not useon damaged or broken skin.
When using this product■ keep out of eyes. Rinse eyes with water
to remove.
Stop use and ask a doctor ifrash occurs.

Keep out of reach of children. If swallowed, get medical help or contact a Polson Control Center right away.

Inactive ingredients

C12-15 Alkyl Benzoate
Caprylic/Capric Triglyceride
Cetyl Alcohol
Dimethicone
Ethylhexyl Methoxycrylene
Euphorbia Cerifera (Candililla) Wax
Humulus Lupulus (Hops) Extract
Lauric Acid
Myristic Acid
Neopentyl Glycol Diethylhexanoate
Ozokerite
Palmitic Acid
Polyethylene
Silica
Stearic Acid
Synthetic Beeswax